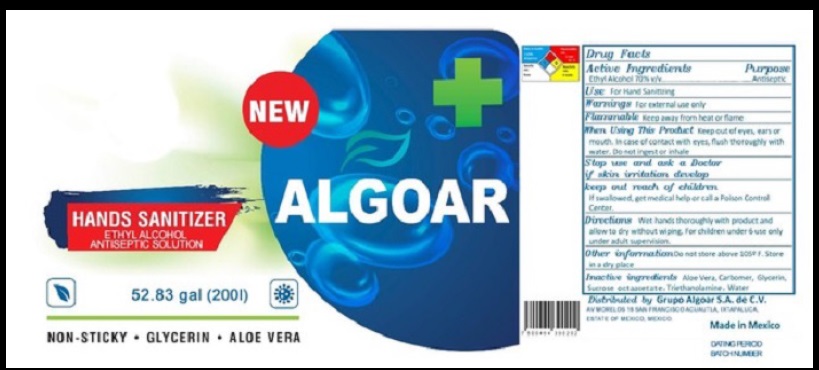 DRUG LABEL: ALGOAR Hand Sanitizer
NDC: 78884-001 | Form: GEL
Manufacturer: Grupo Algoar de Mexico, S.A. de C.V.
Category: otc | Type: HUMAN OTC DRUG LABEL
Date: 20200625

ACTIVE INGREDIENTS: ALCOHOL 70 mL/100 mL
INACTIVE INGREDIENTS: WATER; CARBOMER HOMOPOLYMER, UNSPECIFIED TYPE; GLYCERIN; ALOE VERA LEAF; TROLAMINE; SUCROSE OCTAACETATE

Active Ingredient

Ethyl Alcohol 70% v/v.

Purpose

Antiseptic

Uses

For hand sanitizing

Warnings

For external use only. Flammable. Keep away from heat or flame.

When using this product keep out of eyes, ears, and mouth. In case of contact with eyes, rinse eyes thoroughly with water. Do not inhale or ingest.
Stop use and ask a doctor if irritation develop.

Keep out of reach of children. If swallowed, get medical help or call a Poison Control Center.

Directions

- Wet hands thoroughly with product and allow to dry without wiping.
- For children under 6 use only under adult supervision.

Other information

- Do not store above 40C (104F). Store in a dry place.

Inactive ingredients

Water, Glycerin, Carbomer, Aloe vera, Triethanolamine, sucrose octaacetate